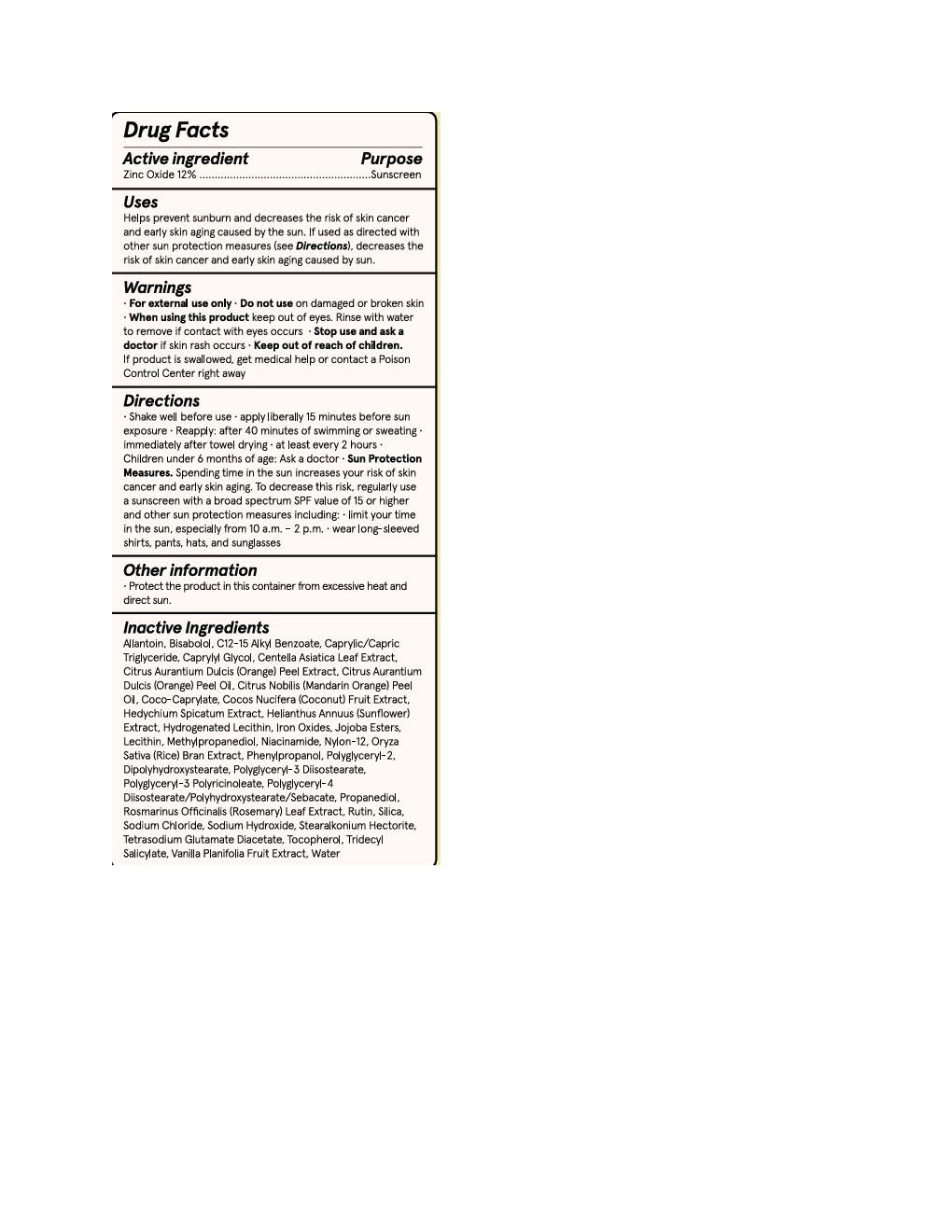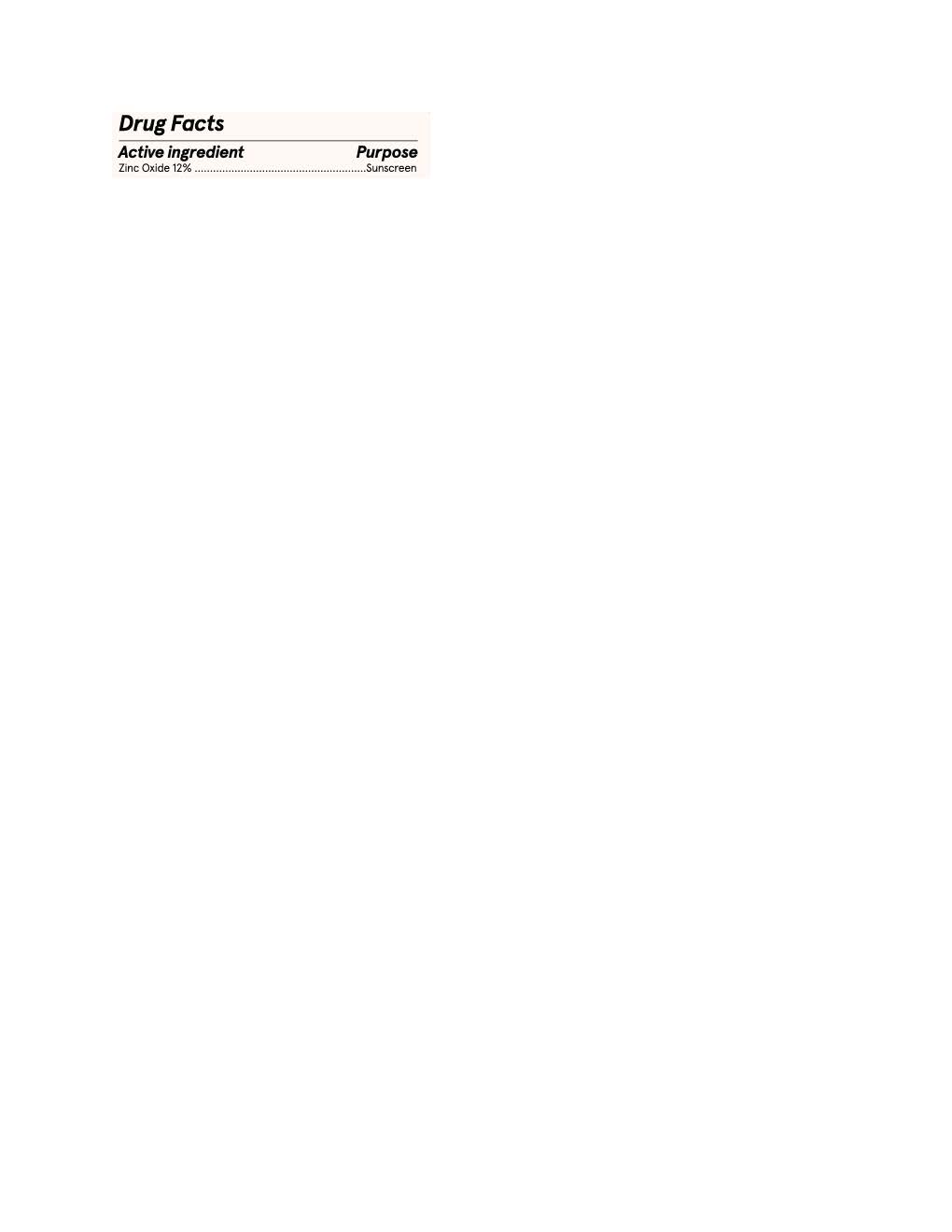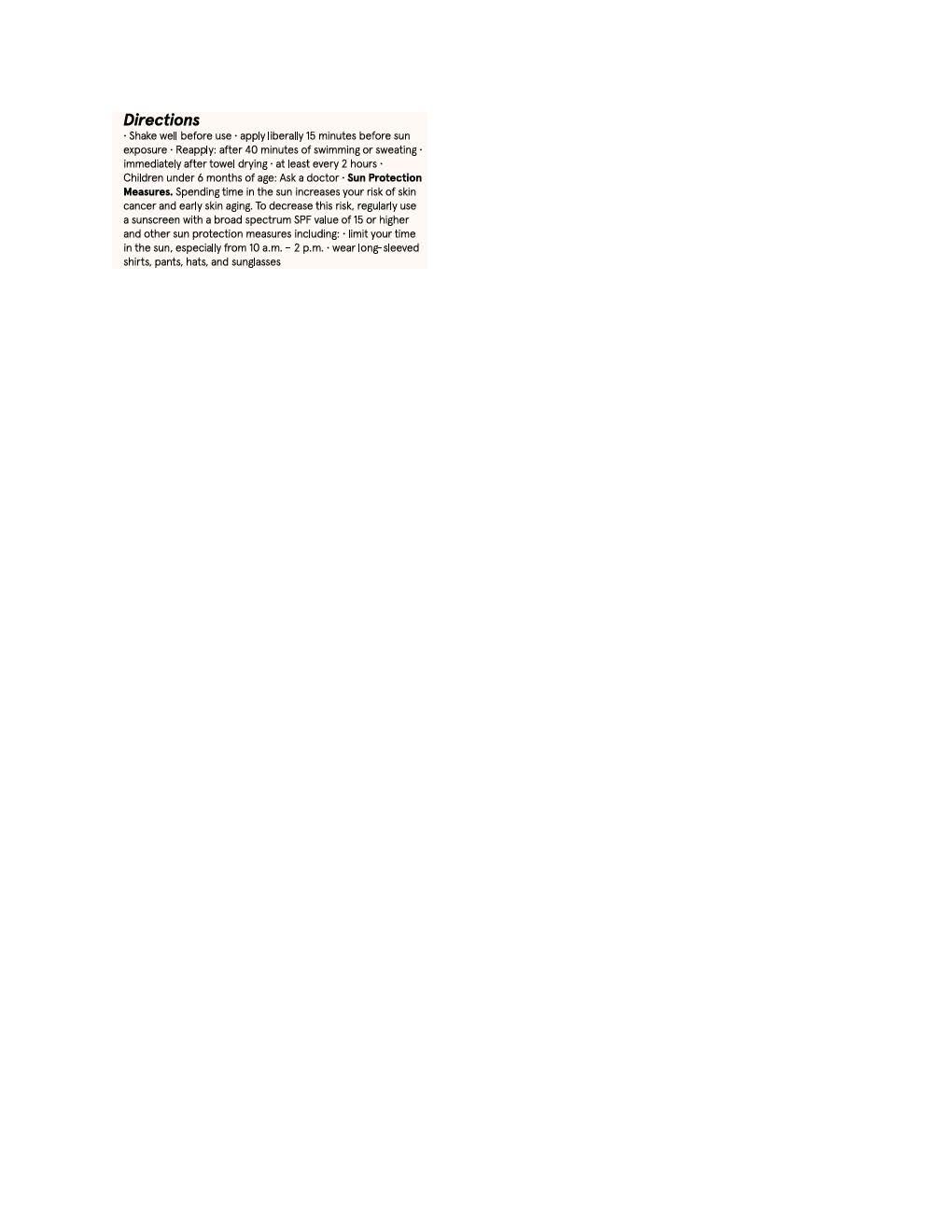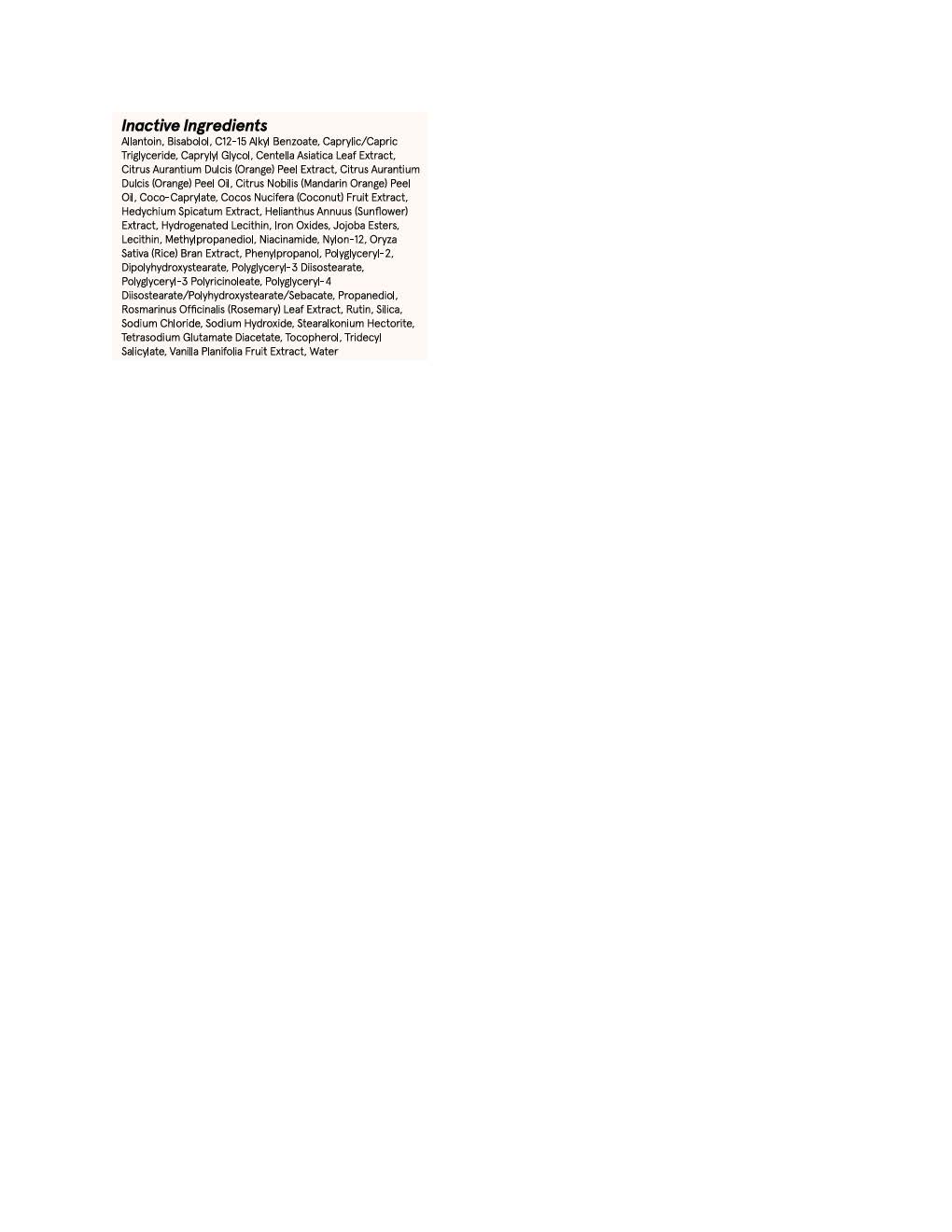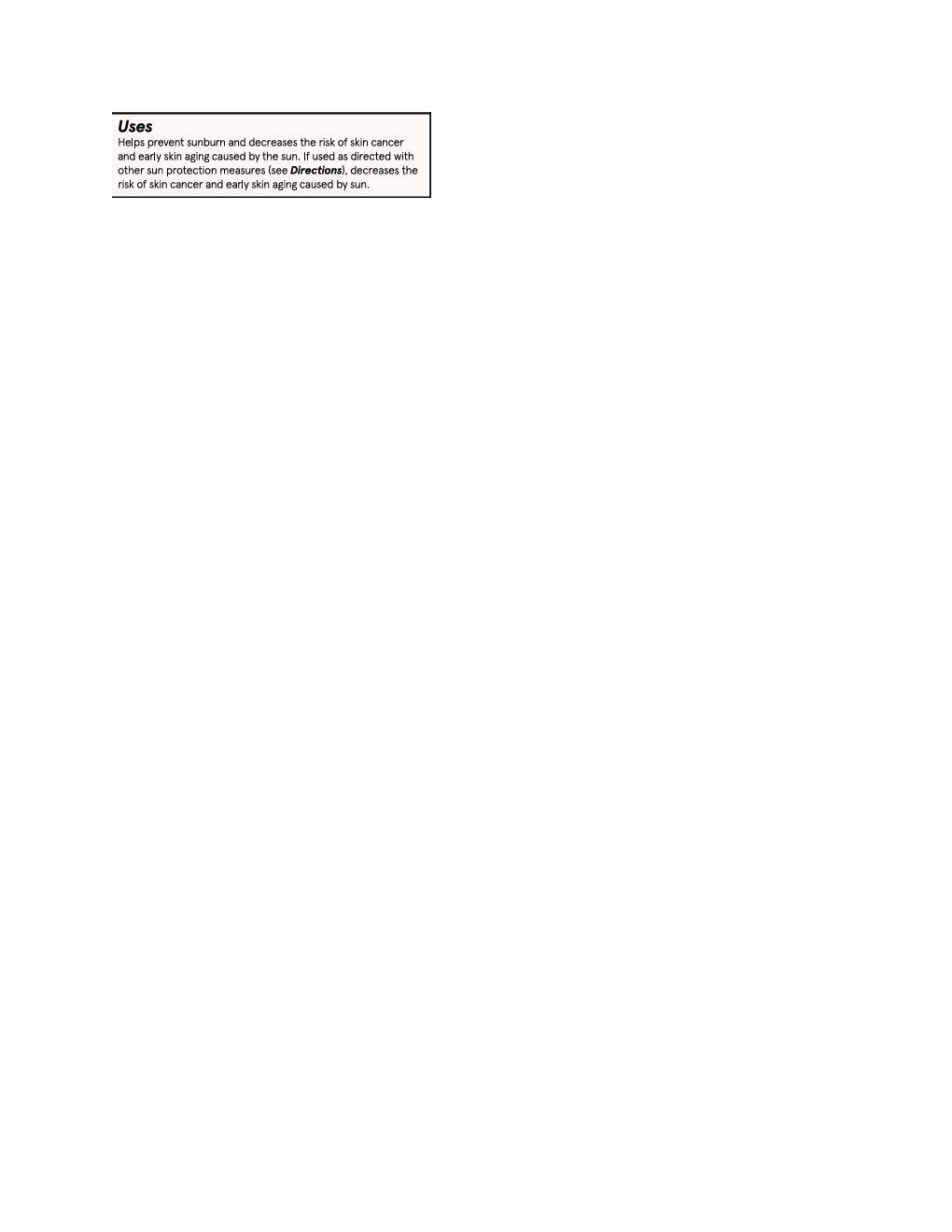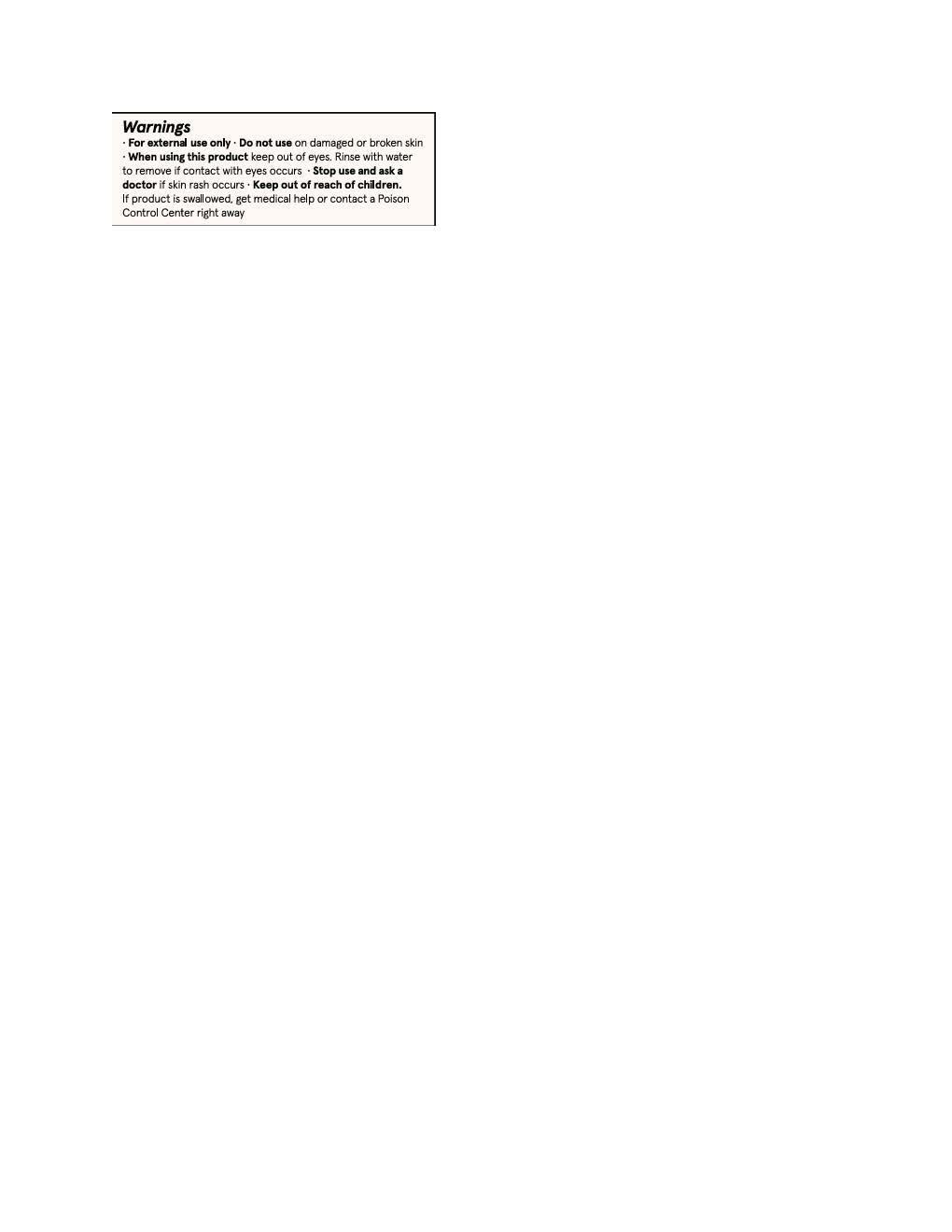 DRUG LABEL: Blume Sunburst Sunscreen
NDC: 83656-2106 | Form: LOTION
Manufacturer: Blume
Category: otc | Type: HUMAN OTC DRUG LABEL
Date: 20251015

ACTIVE INGREDIENTS: ZINC OXIDE 132 mg/1 mL
INACTIVE INGREDIENTS: PHENYLPROPANOL; STEARALKONIUM HECTORITE; FERROUS OXIDE; CENTELLA ASIATICA LEAF; JOJOBA OIL; ORYZA SATIVA WHOLE; TRIDECYL SALICYLATE; SILICON DIOXIDE; TOCOPHEROL; CAPRYLYL GLYCOL; COCO-CAPRYLATE; NYLON-12; LECITHIN, SOYBEAN; METHYLPROPANEDIOL; POLYGLYCERYL-2 DIPOLYHYDROXYSTEARATE; ALLANTOIN; ALKYL (C12-15) BENZOATE; ROSMARINUS OFFICINALIS FLOWER; .ALPHA.-BISABOLOL, (+)-; SODIUM HYDROXIDE; WATER; NIACINAMIDE; PROPANEDIOL; TETRASODIUM GLUTAMATE DIACETATE; SODIUM CHLORIDE; POLYGLYCERYL-4 DIISOSTEARATE/POLYHYDROXYSTEARATE/SEBACATE; POLYGLYCERYL-3 DIISOSTEARATE; RUTIN

Blume Sunburst Sunscreen